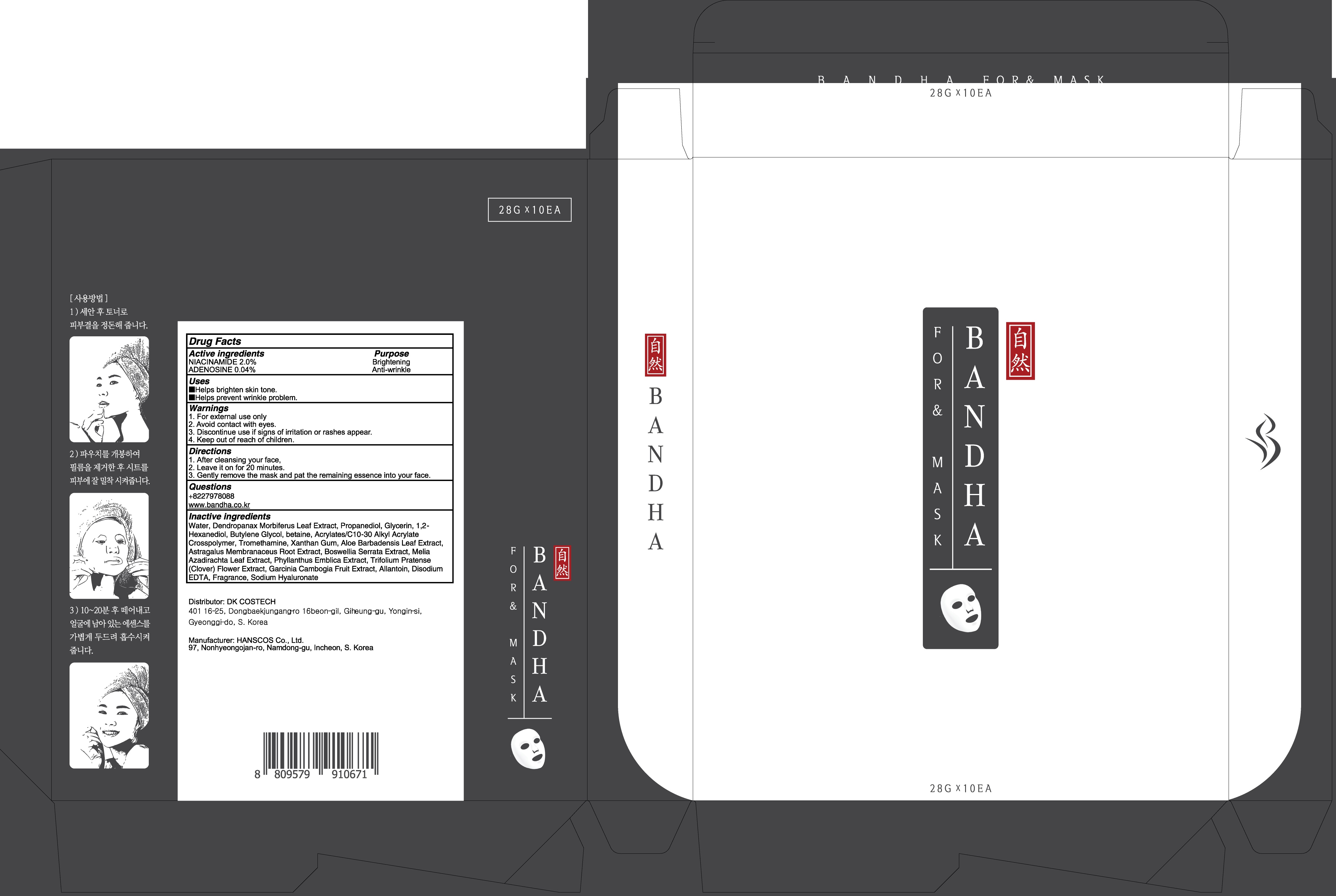 DRUG LABEL: BANDHA FOR AND MASK
NDC: 80623-010 | Form: PATCH
Manufacturer: DKCOSTECH
Category: otc | Type: HUMAN OTC DRUG LABEL
Date: 20200923

ACTIVE INGREDIENTS: NIACINAMIDE 0.56 g/28 g; ADENOSINE 0.01 g/28 g
INACTIVE INGREDIENTS: Water; Propanediol; Glycerin

ACTIVE INGREDIENTS

NIACINAMIDE 2.0%
ADENOSINE 0.04%

INACTIVE INGREDIENTS

Water, Dendropanax Morbiferus Leaf Extract, Propanediol, Glycerin, 1,2-Hexanediol, Butylene Glycol, betaine, Acrylates/C10-30 Alkyl Acrylate Crosspolymer, Tromethamine, Xanthan Gum, Aloe Barbadensis Leaf Extract, Astragalus Membranaceus Root Extract, Boswellia Serrata Extract, Melia Azadirachta Leaf Extract, Phyllanthus Emblica Extract, Trifolium Pratense (Clover) Flower Extract, Garcinia Cambogia Fruit Extract, Allantoin, Disodium EDTA, Fragrance, Sodium Hyaluronate

PURPOSE

Brightening
Anti-wrinkle

WARNINGS

1. For external use only
2. Avoid contact with eyes.
3. Discontinue use if signs of irritation or rashes appear.
4. Keep out of reach of children.

KEEP OUT OF REACH OF CHILDREN

Uses

■ Helps brighten skin tone.
■ Helps prevent wrinkle problem.

Directions

1. After cleansing your face,
2. Leave it on for 20 minutes.
3. Gently remove the mask and pat the remaining essence into your face.

QUESTIONS

+8227978088
www.bandha.co.kr